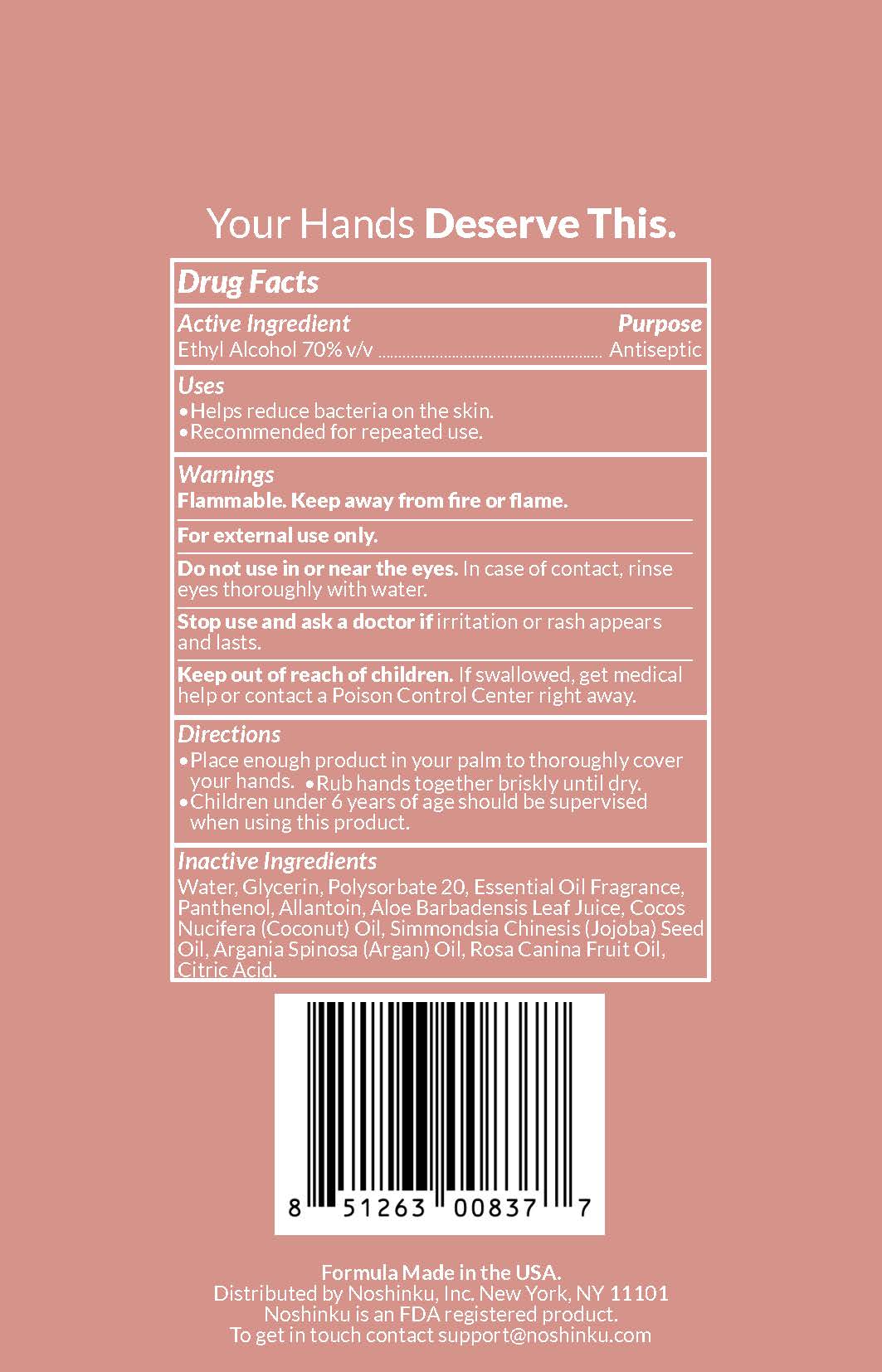 DRUG LABEL: Nourishing Hand Sanitizer Orange Coriander
NDC: 73898-008 | Form: SOLUTION
Manufacturer: Noshinku
Category: otc | Type: HUMAN OTC DRUG LABEL
Date: 20251031

ACTIVE INGREDIENTS: ALCOHOL 70 mL/100 mL
INACTIVE INGREDIENTS: ALOE VERA LEAF; ARGAN OIL; CITRIC ACID; GLYCERIN; ALLANTOIN; COCONUT OIL; JOJOBA OIL; PANTHENOL; POLYSORBATE 20; ROSA CANINA FRUIT OIL; WATER

Noshinku Orange Coriander Hand Sanitizer (73898-008)

Active Ingredients

ETHYL ALCOHOL 70% V/V

Purpose

ANTISEPTIC

Uses

HELPS REDUCE BACTERIA ON THE SKIN.
RECOMMENDED FOR REPEATED USE.

Warnings

FLAMMABLE. KEEP AWAY FROM FIRE OR FLAME.

FOR EXTERNAL USE ONLY.

DO NOT USE

IN OR NEAR THE EYES. IN CASE OF CONTACT, RINSE EYES THOROUGHLY WITH WATER.

STOP USE

AND CONSULT A DOCTOR IF IRRITATION OR RASH APPEARS AND LASTS.

KEEP OUT OF REACH OF CHILDREN.

IF SWALLOWED, GET MEDICAL HELP OR CONTACT POISON CONTROL CENTER RIGHT AWAY.

Directions

Place enough product in your palm to thoroughly cover your hands.
Rub hands together briskly until dry.
Children under 6 years of age should be supervised when using this product.

Inactive Ingredients

Water, Glycerin, Polysorbate 20, Essential Oil Fragrance, Panthenol, Allantoin, Aloe Barbadensis Leaf Juice, Cocos Nucifera (Coconut) Oil, Simmondsia Chinesis (Jojoba) Seed Oil, Argania Spinosa (Argan) Oil, Rosa Canina Fruit Oil, Citric Acid.